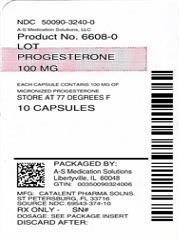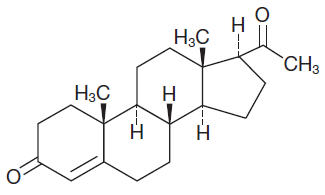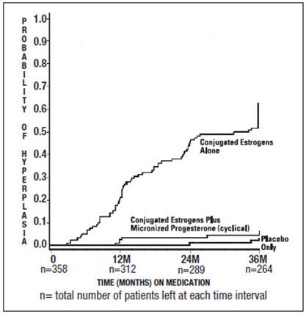 DRUG LABEL: Progesterone
NDC: 50090-3240 | Form: CAPSULE
Manufacturer: A-S Medication Solutions
Category: prescription | Type: HUMAN PRESCRIPTION DRUG LABEL
Date: 20210416

ACTIVE INGREDIENTS: PROGESTERONE 100 mg/1 1
INACTIVE INGREDIENTS: PEANUT OIL; GELATIN, UNSPECIFIED; GLYCERIN; LECITHIN, SOYBEAN; TITANIUM DIOXIDE; D&C YELLOW NO. 10; FD&C RED NO. 40

Progesterone, USP

Capsules 100 mg

Capsules 200 mg
Rx only

WARNING: CARDIOVASCULAR DISORDERS, BREAST CANCER AND PROBABLE DEMENTIA FOR ESTROGEN PLUS PROGESTIN THERAPY

Cardiovascular Disorders and Probable Dementia

Estrogens plus progestin therapy should not be used for the prevention of cardiovascular disease or dementia. (See CLINICAL STUDIES and WARNINGS, Cardiovascular disorders and Probable dementia.)

The Women's Health Initiative (WHI) estrogen plus progestin substudy reported increased risks of deep vein thrombosis, pulmonary embolism, stroke and myocardial infarction in postmenopausal women (50 to 79 years of age) during 5.6 years of treatment with daily oral conjugated estrogens (CE) [0.625 mg] combined with medroxyprogesterone acetate (MPA) [2.5 mg], relative to placebo. (See CLINICAL STUDIES and WARNINGS, Cardiovascular disorders.)

The WHI Memory Study (WHIMS) estrogen plus progestin ancillary study of the WHI reported an increased risk of developing probable dementia in postmenopausal women 65 years of age or older during 4 years of treatment with daily CE (0.625 mg) combined with MPA (2.5 mg), relative to placebo. It is unknown whether this finding applies to younger postmenopausal women. (See CLINICAL STUDIES and WARNINGS, Probable dementia and PRECAUTIONS, Geriatric Use.)

Breast Cancer

The WHI estrogen plus progestin substudy also demonstrated an increased risk of invasive breast cancer. (See CLINICAL STUDIES and WARNINGS, Malignant neoplasms, Breast Cancer.)

In the absence of comparable data, these risks should be assumed to be similar for other doses of CE and MPA, and other combinations and dosage forms of estrogens and progestins. Progestins with estrogens should be prescribed at the lowest effective doses and for the shortest duration consistent with treatment goals and risks for the individual woman.

DESCRIPTION

Progesterone, USP Capsules contain micronized progesterone for oral administration. Progesterone has a molecular weight of 314.47 and a molecular formula of C21H30O2. Progesterone (pregn-4-ene-3, 20-dione) is a white or creamy white, odorless, crystalline powder practically insoluble in water, soluble in alcohol, acetone and dioxane and sparingly soluble in vegetable oils, stable in air, melting between 126° and 131°C. The structural formula is:

Progesterone is synthesized from a starting material from a plant source and is chemically identical to progesterone of human ovarian origin. Progesterone, USP Capsules are available in multiple strengths to afford dosage flexibility for optimum management. Progesterone, USP Capsules contain 100 mg or 200 mg micronized progesterone.

The inactive ingredients for Progesterone, USP Capsules 100 mg include: peanut oil NF, gelatin NF, glycerin USP, lecithin NF, titanium dioxide USP, FD&C Red No. 40, and D&C Yellow No. 10.

The inactive ingredients for Progesterone, USP Capsules 200 mg include: peanut oil NF, gelatin NF, glycerin USP, lecithin NF, titanium dioxide USP, D&C Yellow No. 10, and FD&C Yellow No. 6.

CLINICAL PHARMACOLOGY

Progesterone, USP Capsules are an oral dosage form of micronized progesterone which is chemically identical to progesterone of ovarian origin. The oral bioavailability of progesterone is increased through micronization.

Pharmacokinetics

A. Absorption

After oral administration of progesterone as a micronized soft-gelatin capsule formulation, maximum serum concentrations were attained within 3 hours. The absolute bioavailability of micronized progesterone is not known. Table 1 summarizes the mean pharmacokinetic parameters in postmenopausal women after five oral daily doses of Progesterone, USP Capsules 100 mg as a micronized soft-gelatin capsule formulation.

TABLE 1. Pharmacokinetic Parameters of Progesterone, USP Capsules
Parameter | Progesterone, USP Capsules Daily Dose
Parameter | 100 mg | 200 mg | 300 mg
Cmax (ng/mL) | 17.3 ± 21.9 [Mean ± S.D.] | 38.1 ± 37.8 | 60.6 ± 72.5
Tmax (hr) | 1.5 ± 0.8 | 2.3 ± 1.4 | 1.7 ± 0.6
AUC (0-10) (ng × hr/mL) | 43.3 ± 30.8 | 101.2 ± 66.0 | 175.7 ± 170.3

Serum progesterone concentrations appeared linear and dose proportional following multiple dose administration of Progesterone, USP Capsules 100 mg over the dose range 100 mg per day to 300 mg per day in postmenopausal women. Although doses greater than 300 mg per day were not studied in females, serum concentrations from a study in male volunteers appeared linear and dose proportional between 100 mg per day and 400 mg per day. The pharmacokinetic parameters in male volunteers were generally consistent with those seen in postmenopausal women.

B. Distribution

Progesterone is approximately 96 percent to 99 percent bound to serum proteins, primarily to serum albumin (50 to 54 percent) and transcortin (43 to 48 percent).

C. Metabolism

Progesterone is metabolized primarily by the liver largely to pregnanediols and pregnanolones. Pregnanediols and pregnanolones are conjugated in the liver to glucuronide and sulfate metabolites. Progesterone metabolites which are excreted in the bile may be deconjugated and may be further metabolized in the intestine via reduction, dehydroxylation, and epimerization.

D. Excretion

The glucuronide and sulfate conjugates of pregnanediol and pregnanolone are excreted in the bile and urine. Progesterone metabolites are eliminated mainly by the kidneys. Progesterone metabolites which are excreted in the bile may undergo enterohepatic recycling or may be excreted in the feces.

E. Special Populations

The pharmacokinetics of Progesterone, USP Capsules have not been assessed in low body weight or obese patients.

Hepatic Insufficiency: The effect of hepatic impairment on the pharmacokinetics of Progesterone, USP Capsules has not been studied.

Renal Insufficiency: The effect of renal impairment on the pharmacokinetics of Progesterone, USP Capsules has not been studied.

F. Food–Drug Interaction

Concomitant food ingestion increased the bioavailability of Progesterone, USP Capsules relative to a fasting state when administered to postmenopausal women at a dose of 200 mg.

G. Drug Interactions

The metabolism of progesterone by human liver microsomes was inhibited by ketoconazole (IC50 < 0.1 μM). Ketoconazole is a known inhibitor of cytochrome P450 3A4, hence these data suggest that ketoconazole or other known inhibitors of this enzyme may increase the bioavailability of progesterone. The clinical relevance of the in vitro findings is unknown.

Coadministration of conjugated estrogens and Progesterone, USP Capsules to 29 postmenopausal women over a 12-day period resulted in an increase in total estrone concentrations (Cmax 3.68 ng/mL to 4.93 ng/mL) and total equilin concentrations (Cmax 2.27 ng/mL to 3.22 ng/mL) and a decrease in circulating 17β estradiol concentrations (Cmax 0.037 ng/mL to 0.030 ng/mL). The half-life of the conjugated estrogens was similar with coadministration of Progesterone, USP Capsules. Table 2 summarizes the pharmacokinetic parameters.

TABLE 2. Mean (± S.D.) Pharmacokinetic Parameters for Estradiol, Estrone, and Equilin Following Coadministration of Conjugated Estrogens 0.625 mg and Progesterone, USP Capsules, 200 mg for 12 Days to Postmenopausal Women
 | Conjugated Estrogens |  |  | Conjugated Estrogens plus Progesterone, USP Capsules
Drug | Cmax (ng/mL) | Tmax (hr) | AUC(0-24h) (ng × h/mL) | Cmax (ng/mL) | Tmax (hr) | AUC(0-24h) (ng × h/mL)
Estradiol | 0.037 ± 0.048 | 12.7 ± 9.1 | 0.676 ± 0.737 | 0.030 ± 0.032 | 17.32 ± 1.21 | 0.561 ± 0.572
Estrone Total [Total estrogens is the sum of conjugated and unconjugated estrogen.] | 3.68 ± 1.55 | 10.6 ± 6.8 | 61.3 ± 26.36 | 4.93 ± 2.07 | 7.5 ± 3.8 | 85.9 ± 41.2
Equilin Total | 2.27 ± 0.95 | 6.0 ± 4.0 | 28.8 ± 13.0 | 3.22 ± 1.13 | 5.3 ± 2.6 | 38.1 ± 20.2

CLINICAL STUDIES

Effects on the endometrium

In a randomized, double-blind clinical trial, 358 postmenopausal women, each with an intact uterus, received treatment for up to 36 months. The treatment groups were: Progesterone, USP Capsules at the dose of 200 mg per day for 12 days per 28-day cycle in combination with conjugated estrogens 0.625 mg per day (n=120); conjugated estrogens 0.625 mg per day only (n=119); or placebo (n=119). The subjects in all three treatment groups were primarily Caucasian women (87 percent or more of each group). The results for the incidence of endometrial hyperplasia in women receiving up to 3 years of treatment are shown in Table 3. A comparison of the Progesterone, USP Capsules plus conjugated estrogens treatment group to the conjugated estrogens only group showed a significantly lower rate of hyperplasia (6 percent combination product versus 64 percent estrogen alone) in the Progesterone, USP Capsules plus conjugated estrogens treatment group throughout 36 months of treatment.

TABLE 3. Incidence of Endometrial Hyperplasia in Women Receiving 3 Years of Treatment
Endometrial Diagnosis | Treatment Group
 | Conjugated Estrogens 0.625 mg + Progesterone, USP Capsules 200 mg (cyclical) |  | Conjugated Estrogens 0.625 mg (alone) |  | Placebo
 | Number of patients | % of patients | Number of patients | % of patients | Number of patients | % of patients
 | n=117 |  | n=115 |  | n=116
HYPERPLASIA [Most advanced result to least advanced result: Adenocarcinoma > atypical hyperplasia > complex hyperplasia > simple hyperplasia] | 7 | 6 | 74 | 64 | 3 | 3
Adenocarcinoma | 0 | 0 | 0 | 0 | 1 | 1
Atypical hyperplasia | 1 | 1 | 14 | 12 | 0 | 0
Complex hyperplasia | 0 | 0 | 27 | 23 | 1 | 1
Simple hyperplasia | 6 | 5 | 33 | 29 | 1 | 1

The times to diagnosis of endometrial hyperplasia over 36 months of treatment are shown in Figure 1. This figure illustrates graphically that the proportion of patients with hyperplasia was significantly greater for the conjugated estrogens group (64 percent) compared to the conjugated estrogens plus Progesterone, USP Capsules group (6 percent).

Figure 1. Time to Hyperplasia in Women Receiving up to 36 Months of Treatment

The discontinuation rates due to hyperplasia over the 36 months of treatment are as shown in Table 4. For any degree of hyperplasia, the discontinuation rate for patients who received conjugated estrogens plus Progesterone, USP Capsules was similar to that of the placebo only group, while the discontinuation rate for patients who received conjugated estrogens alone was significantly higher. Women who permanently discontinued treatment due to hyperplasia were similar in demographics to the overall study population.

TABLE 4. Discontinuation Rate Due to Hyperplasia Over 36 Months of Treatment
Most Advanced Biopsy Result Through 36 Months of Treatment | Treatment Group
 | Conjugated Estrogens + Progesterone, USP Capsules (cyclical) |  | Conjugated Estrogens (alone) |  | Placebo
 | n=120 |  | n=119 |  | n=119
 | Number of patients | % of patients | Number of patients | % of patients | Number of patients | % of patients
Adenocarcinoma | 0 | 0 | 0 | 0 | 1 | 1
Atypical hyperplasia | 1 | 1 | 10 | 8 | 0 | 0
Complex hyperplasia | 0 | 0 | 21 | 18 | 1 | 1
Simple hyperplasia | 1 | 1 | 13 | 11 | 0 | 0

Effects on secondary amenorrhea

In a single-center, randomized, double-blind clinical study that included premenopausal women with secondary amenorrhea for at least 90 days, administration of 10 days of Progesterone, USP Capsules therapy resulted in 80 percent of women experiencing withdrawal bleeding within 7 days of the last dose of Progesterone, USP Capsules, 300 mg per day (n=20), compared to 10 percent of women experiencing withdrawal bleeding in the placebo group (n=21).

In a multicenter, parallel-group, open label, postmarketing dosing study that included premenopausal women with secondary amenorrhea for at least 90 days, administration of 10 days of Progesterone, USP Capsules during two 28-day treatment cycles, 300 mg per day (n=107) or 400 mg per day (n=99), resulted in 73.8 percent and 76.8 percent of women, respectively, experiencing withdrawal bleeding.

The rate of secretory transformation was evaluated in a multicenter, randomized, double-blind clinical study in estrogen-primed postmenopausal women. Progesterone, USP Capsules administered orally for 10 days at 400 mg per day (n=22) induced complete secretory changes in the endometrium in 45 percent of women compared to 0 percent in the placebo group (n=23).

A second multicenter, parallel-group, open label postmarketing dosing study in premenopausal women with secondary amenorrhea for at least 90 days also evaluated the rate of secretory transformation. All subjects received daily oral conjugated estrogens over 3 consecutive 28-day treatment cycles and Progesterone, USP Capsules, 300 mg per day (n=107) or 400 mg per day (n=99) for 10 days of each treatment cycle. The rate of complete secretory transformation was 21.5 percent and 28.3 percent, respectively.

Women's Health Initiative Studies

The Women's Health Initiative (WHI) enrolled approximately 27,000 predominantly healthy postmenopausal women in two substudies to assess the risks and benefits of daily oral conjugated estrogens (CE) [0.625 mg]-alone or in combination with medroxyprogesterone acetate (MPA) [2.5 mg] compared to placebo in the prevention of certain chronic diseases. The primary endpoint was the incidence of coronary heart disease [(CHD) defined as nonfatal myocardial infarction (MI), silent MI and CHD death], with invasive breast cancer as the primary adverse outcome. A "global index" included the earliest occurrence of CHD, invasive breast cancer, stroke, pulmonary embolism (PE), endometrial cancer (only in the CE plus MPA substudy), colorectal cancer, hip fracture, or death due to other cause. These sub studies did not evaluate the effects of CE–alone or CE plus MPA on menopausal symptoms.

WHI Estrogen Plus Progestin Substudy

The WHI estrogen plus progestin substudy was stopped early. According to the predefined stopping rule, after an average follow-up of 5.6 years of treatment, the increased risk of breast cancer and cardiovascular events exceeded the specified benefits included in the "global index." The absolute excess risk of events in the "global index" was 19 per 10,000 women-years.

For those outcomes included in the WHI "global index" that reached statistical significance after 5.6 years of follow-up, the absolute excess risks per 10,000 women-years in the group treated with CE plus MPA were 7 more CHD events, 8 more strokes, 10 more PEs, and 8 more invasive breast cancers, while the absolute risk reductions per 10,000 women-years were 6 fewer colorectal cancers and 5 fewer hip fractures.

Results of the estrogen plus progestin substudy, which included 16,608 women (average 63 years of age, range 50 to 79; 83.9 percent White, 6.8 percent Black, 5.4 percent Hispanic, 3.9 percent Other) are presented in Table 5. These results reflect centrally adjudicated data after an average follow-up of 5.6 years.

TABLE 5. Relative and Absolute Risk Seen in the Estrogen Plus Progestin Substudy of WHI at an Average of 5.6 Years [Adapted from numerous WHI publications. WHI publications can be viewed at www.nhlbi.nih.gov/whi.] , [Results are based on centrally adjudicated data.]
Event | Relative Risk CE/MPA versus Placebo (95% nCI [Nominal confidence intervals unadjusted for multiple looks and multiple comparisons.]) | CE/MPA n = 8,506 | Placebo n = 8,102
Event | Relative Risk CE/MPA versus Placebo (95% nCI [Nominal confidence intervals unadjusted for multiple looks and multiple comparisons.]) | Absolute Risk per 10,000 Women-Years
CHD events | 1.23 (0.99-1.53) | 41 | 34
Non-fatal MI | 1.28 (1.00-1.63) | 31 | 25
CHD death | 1.10 (0.70-1.75) | 8 | 8
All stroke | 1.31 (1.03-1.88) | 33 | 25
Ischemic Stroke | 1.44 (1.09-1.90) | 26 | 18
Deep vein thrombosis [Not included in Global Index.] | 1.95 (1.43-2.67) | 26 | 13
Pulmonary embolism | 2.13 (1.45-3.11) | 18 | 8
Invasive breast cancer [Includes metastatic and non-metastatic breast cancer with the exception of in situ breast cancer.] | 1.24 (1.01-1.54) | 41 | 33
Colorectal cancer | 0.61 (0.42-0.87) | 10 | 16
Endometrial cancer | 0.81 (0.48-1.36) | 6 | 7
Cervical cancer | 1.44 (0.47-4.42) | 2 | 1
Hip fracture | 0.67 (0.47-0.96) | 11 | 16
Vertebral fractures | 0.65 (0.46-0.92) | 11 | 17
Lower arm/wrist fractures | 0.71 (0.59-0.85) | 44 | 62
Total fractures | 0.76 (0.69-0.83) | 152 | 199
Overall mortality [All deaths, except from breast or colorectal cancer, definite or probable CHD, PE or cerebrovascular disease.] | 1.00 (0.83-1.19) | 52 | 52
Global Index [A subset of the events was combined in a "global index" defined as the earliest occurrence of CHD events, invasive breast cancer, stroke, pulmonary embolism, endometrial cancer, colorectal cancer, hip fracture, or death due to other causes.] | 1.13 (1.02-1.25) | 184 | 165

Timing of the initiation of estrogen plus progestin therapy relative to the start of menopause may affect the overall risk benefit profile. The WHI estrogen plus progestin substudy stratified for age showed in women 50 to 59 years of age a non-significant trend toward reducing risk of overall mortality [hazard ratio (HR) 0.69 (95 percent CI, 0.44-1.07)].

Women's Health Initiative Memory Study

The estrogen plus progestin Women's Health Initiative Memory Study (WHIMS), an ancillary study of WHI, enrolled 4,532 predominantly healthy postmenopausal women 65 years of age and older (47 percent were 65 to 69 years of age; 35 percent were 70 to 74 years of age; and 18 percent were 75 years of age and older) to evaluate the effects of daily CE (0.625 mg) plus MPA (2.5 mg) on the incidence of probable dementia (primary outcome) compared to placebo.

After an average follow-up of 4 years, the relative risk of probable dementia for CE plus MPA versus placebo was 2.05 (95 percent CI, 1.21 – 3.48). The absolute risk of probable dementia for CE plus MPA versus placebo was 45 versus 22 per 10,000 women-years. Probable dementia as defined in this study included Alzheimer's disease (AD), vascular dementia (VaD) and mixed type (having features of both AD and VaD). The most common classification of probable dementia in the treatment group and the placebo group was AD. Since the ancillary study was conducted in women 65 to 79 years of age, it is unknown whether these findings apply to younger postmenopausal women. (See WARNINGS, Probable dementia and PRECAUTIONS, Geriatric Use.)

INDICATIONS AND USAGE

Progesterone, USP Capsules are indicated for use in the prevention of endometrial hyperplasia in nonhysterectomized postmenopausal women who are receiving conjugated estrogens tablets. They are also indicated for use in secondary amenorrhea.

CONTRAINDICATIONS

Progesterone, USP Capsules should not be used in women with any of the following conditions:

1. Progesterone, USP Capsules should not be used in patients with known hypersensitivity to its ingredients. Progesterone, USP Capsules contain peanut oil and should never be used by patients allergic to peanuts.
2. Undiagnosed abnormal genital bleeding.
3. Known, suspected, or history of breast cancer.
4. Active deep vein thrombosis, pulmonary embolism or history of these conditions.
5. Active arterial thromboembolic disease (for example, stroke and myocardial infarction), or a history of these conditions.
6. Known liver dysfunction or disease.
7. Known or suspected pregnancy.

WARNINGS

See BOXED WARNING.

1. Cardiovascular disorders

An increased risk of pulmonary embolism, deep vein thrombosis (DVT), stroke, and myocardial infarction has been reported with estrogen plus progestin therapy. Should any of these occur or be suspected, estrogen with progestin therapy should be discontinued immediately.

Risk factors for arterial vascular disease (for example, hypertension, diabetes mellitus, tobacco use, hypercholesterolemia, and obesity) and/or venous thromboembolism (for example, personal history or family history of venous thromboembolism [VTE], obesity, and systemic lupus erythematosus) should be managed appropriately.

a. Stroke

In the Women's Health Initiative (WHI) estrogen plus progestin substudy, a statistically significant increased risk of stroke was reported in women 50 to 79 years of age receiving daily CE (0.625 mg) plus MPA (2.5 mg) compared to women in the same age group receiving placebo (33 versus 25 per 10,000 women-years). The increase in risk was demonstrated after the first year and persisted. (See CLINICAL STUDIES.) Should a stroke occur or be suspected, estrogen plus progestin therapy should be discontinued immediately.

b. Coronary Heart Disease

In the WHI estrogen plus progestin substudy, there was a statistically non-significant increased risk of coronary heart disease (CHD) events (defined as nonfatal myocardial infarction [MI], silent MI, or CHD death) reported in women receiving daily CE (0.625 mg) plus MPA (2.5 mg) compared to women receiving placebo (41 versus 34 per 10,000 women-years). An increase in relative risk was demonstrated in year 1 and a trend toward decreasing relative risk was reported in years 2 through 5. (See CLINICAL STUDIES.)

In postmenopausal women with documented heart disease (n = 2,763, average age 66.7 years), in a controlled clinical trial of secondary prevention of cardiovascular disease (Heart and Estrogen/Progestin Replacement Study [HERS]), treatment with daily CE (0.625 mg) plus MPA (2.5 mg) demonstrated no cardiovascular benefit. During an average follow-up of 4.1 years, treatment with CE plus MPA did not reduce the overall rate of CHD events in postmenopausal women with established coronary heart disease. There were more CHD events in the CE plus MPA-treated group than in the placebo group in year 1, but not during the subsequent years. Two thousand, three hundred and twenty-one (2,321) women from the original HERS trial agreed to participate in an open-label extension of HERS, HERS II. Average follow-up in HERS II was an additional 2.7 years, for a total of 6.8 years overall. Rates of CHD events were comparable among women in the CE plus MPA group and the placebo group in HERS, HERS II, and overall.

c. Venous Thromboembolism

In the WHI estrogen plus progestin substudy, a statistically significant 2-fold greater rate of VTE (DVT and pulmonary embolism [PE]) was reported in women receiving daily CE (0.625 mg) plus MPA (2.5 mg) compared to women receiving placebo (35 versus 17 per 10,000 women-years). Statistically significant increases in risk for both DVT (26 versus 13 per 10,000 women-years) and PE (18 versus 8 per 10,000 women-years) were also demonstrated. The increase in VTE risk was demonstrated during the first year and persisted. (See CLINICAL STUDIES.) Should a VTE occur or be suspected, estrogen plus progestin therapy should be discontinued immediately.

If feasible, estrogens with progestins should be discontinued at least 4 to 6 weeks before surgery of the type associated with an increased risk of thromboembolism, or during periods of prolonged immobilization.

2. Malignant neoplasms

a. Breast Cancer

The most important randomized clinical trial providing information about breast cancer in estrogen plus progestin users is the Women's Health Initiative (WHI) substudy of daily CE (0.625 mg) plus MPA (2.5 mg). After a mean follow-up of 5.6 years, the estrogen plus progestin substudy reported an increased risk of invasive breast cancer in women who took daily CE plus MPA. In this substudy, prior use of estrogen-alone or estrogen plus progestin therapy was reported by 26 percent of the women. The relative risk of invasive breast cancer was 1.24 (95 percent nCI, 1.01-1.54), and the absolute risk was 41 versus 33 cases per 10,000 women-years, for CE plus MPA compared with placebo.

Among women who reported prior use of hormone therapy, the relative risk of invasive breast cancer was 1.86, and the absolute risk was 46 versus 25 cases per 10,000 women-years, for estrogen plus progestin compared with placebo. Among women who reported no prior use of hormone therapy, the relative risk of invasive breast cancer was 1.09, and the absolute risk was 40 versus 36 cases per 10,000 women-years for CE plus MPA compared with placebo. In the same substudy, invasive breast cancers were larger, were more likely to be node positive, and were diagnosed at a more advanced stage in the CE (0.625 mg) plus MPA (2.5 mg) group compared with the placebo group. Metastatic disease was rare, with no apparent difference between the two groups. Other prognostic factors such as histologic subtype, grade and hormone receptor status did not differ between the groups. (See CLINICAL STUDIES.)

Consistent with the WHI clinical trials, observational studies have also reported an increased risk of breast cancer for estrogen plus progestin therapy, and a smaller increased risk for estrogen-alone therapy, after several years of use. The risk increased with duration of use, and appeared to return to baseline over about 5 years after stopping treatment (only the observational studies have substantial data on risk after stopping). Observational studies also suggest that the risk of breast cancer was greater, and became apparent earlier, with estrogen plus progestin therapy as compared to estrogen-alone therapy. However, these studies have not generally found significant variation in the risk of breast cancer among different estrogen plus progestin combinations, doses, or routes of administration.

The use of estrogen plus progestin has been reported to result in an increase in abnormal mammograms requiring further evaluation. All women should receive yearly breast examinations by a healthcare provider and perform monthly breast self-examinations. In addition, mammography examinations should be scheduled based on patient age, risk factors, and prior mammogram results.

b. Endometrial Cancer

An increased risk of endometrial cancer has been reported with the use of unopposed estrogen therapy in a woman with a uterus. The reported endometrial cancer risk among unopposed estrogen users is about 2 to 12 times greater than in non-users, and appears dependent on duration of treatment and on estrogen dose. Most studies show no significant increased risk associated with the use of estrogens for less than 1 year. The greatest risk appears associated with prolonged use, with increased risks of 15- to 24-fold for 5 to 10 years or more and this risk has been shown to persist for at least 8 to 15 years after estrogen therapy is discontinued.

Clinical surveillance of all women using estrogen plus progestin therapy is important. Adequate diagnostic measures, including directed or random endometrial sampling when indicated, should be undertaken to rule out malignancy in all cases of undiagnosed persistent or recurring abnormal genital bleeding. There is no evidence that the use of natural estrogens results in a different endometrial risk profile than synthetic estrogens of equivalent estrogen dose. Adding a progestin to estrogen therapy in postmenopausal women has been shown to reduce the risk of endometrial hyperplasia, which may be a precursor to endometrial cancer.

c. Ovarian Cancer

The WHI estrogen plus progestin substudy reported a statistically non-significant increased risk of ovarian cancer. After an average follow-up of 5.6 years, the relative risk for ovarian cancer for CE plus MPA versus placebo was 1.58 (95 percent nCI, 0.77 – 3.24). The absolute risk for CE plus MPA versus placebo was 4 versus 3 cases per 10,000 women-years. In some epidemiologic studies, the use of estrogen plus progestin and estrogen-only products, in particular for 5 or more years, has been associated with an increased risk of ovarian cancer. However, the duration of exposure associated with increased risk is not consistent across all epidemiologic studies and some report no association.

3. Probable dementia

In the estrogen plus progestin Women's Health Initiative Memory Study (WHIMS), an ancillary study of WHI, a population of 4,532 postmenopausal women 65 to 79 years of age was randomized to daily CE (0.625 mg) plus MPA (2.5 mg) or placebo.

In the WHIMS estrogen plus progestin ancillary study, after an average follow-up of 4 years, 40 women in the CE plus MPA group and 21 women in the placebo group were diagnosed with probable dementia. The relative risk of probable dementia for estrogen plus progestin versus placebo was 2.05 (95 percent CI, 1.21-3.48). The absolute risk of probable dementia for CE plus MPA versus placebo was 45 versus 22 cases per 10,000 women-years. It is unknown whether these findings apply to younger postmenopausal women. (See CLINICAL STUDIES and PRECAUTIONS, Geriatric Use.)

4. Vision abnormalities

Retinal vascular thrombosis has been reported in patients receiving estrogen. Discontinue estrogen plus progestin therapy pending examination if there is sudden partial or complete loss of vision, or if there is a sudden onset of proptosis, diplopia or migraine. If examination reveals papilledema or retinal vascular lesions, estrogen plus progestin therapy should be permanently discontinued.

PRECAUTIONS

A. General

1. Addition of a progestin when a woman has not had a hysterectomy

Studies of the addition of a progestin for 10 or more days of a cycle of estrogen administration, or daily with estrogen in a continuous regimen, have reported a lowered incidence of endometrial hyperplasia than would be induced by estrogen treatment alone. Endometrial hyperplasia may be a precursor to endometrial cancer.

There are, however, possible risks that may be associated with the use of progestins with estrogens compared with estrogen-alone regimens. These include an increased risk of breast cancer.

2. Fluid Retention

Progesterone may cause some degree of fluid retention. Women with conditions that might be influenced by this factor, such as cardiac or renal dysfunction, warrant careful observation.

3. Dizziness and Drowsiness

Progesterone, USP Capsules may cause transient dizziness and drowsiness and should be used with caution when driving a motor vehicle or operating machinery. Progesterone, USP Capsules should be taken as a single daily dose at bedtime.

B. Patient Information

General: This product contains peanut oil and should not be used if you are allergic to peanuts.

Physicians are advised to discuss the contents of the Patient Information leaflet with patients for whom they prescribe Progesterone, USP Capsules.

C. Drug-Laboratory Test Interactions

The following laboratory results may be altered by the use of estrogen plus progestin therapy:

- Increased sulfobromophthalein retention and other hepatic function tests.
- Coagulation tests: increase in prothrombin factors VII, VIII, IX and X.
- Pregnanediol determination.
- Thyroid function: increase in PBI, and butanol extractable protein bound iodine and decrease in T3 uptake values.

D. Carcinogenesis, Mutagenesis, Impairment of Fertility

Progesterone has not been tested for carcinogenicity in animals by the oral route of administration. When implanted into female mice, progesterone produced mammary carcinomas, ovarian granulosa cell tumors and endometrial stromal sarcomas. In dogs, long-term intramuscular injections produced nodular hyperplasia and benign and malignant mammary tumors. Subcutaneous or intramuscular injections of progesterone decreased the latency period and increased the incidence of mammary tumors in rats previously treated with a chemical carcinogen.

Progesterone did not show evidence of genotoxicity in in vitro studies for point mutations or for chromosomal damage. In vivo studies for chromosome damage have yielded positive results in mice at oral doses of 1000 mg/kg and 2000 mg/kg. Exogenously administered progesterone has been shown to inhibit ovulation in a number of species and it is expected that high doses given for an extended duration would impair fertility until the cessation of treatment.

E. Pregnancy

Progesterone, USP Capsules should not be used during pregnancy. (See CONTRAINDICATIONS).

Pregnancy Category B: Reproductive studies have been performed in mice at doses up to 9 times the human oral dose, in rats at doses up to 44 times the human oral dose, in rabbits at a dose of 10 mcg/day delivered locally within the uterus by an implanted device, in guinea pigs at doses of approximately one-half the human oral dose and in rhesus monkeys at doses approximately the human dose, all based on body surface area, and have revealed little or no evidence of impaired fertility or harm to the fetus due to progesterone.

F. Nursing Women

Detectable amounts of progestin have been identified in the milk of nursing women receiving progestins. Caution should be exercised when Progesterone, USP Capsules are administered to a nursing woman.

G. Pediatric Use

Progesterone, USP Capsules are not indicated in children. Clinical studies have not been conducted in the pediatric population.

H. Geriatric Use

There have not been sufficient numbers of geriatric women involved in clinical studies utilizing Progesterone, USP Capsules to determine whether those over 65 years of age differ from younger subjects in their response to Progesterone, USP Capsules.

The Women's Health Initiative Study

In the Women's Health Initiative (WHI) estrogen plus progestin substudy (daily CE [0.625 mg] plus MPA [2.5 mg] versus placebo), there was a higher relative risk of nonfatal stroke and invasive breast cancer in women greater than 65 years of age. (See CLINICAL STUDIES and WARNINGS, Cardiovascular disorders and Malignant neoplasms.)

The Women's Health Initiative Memory Study

In the Women's Health Initiative Memory Study (WHIMS) of postmenopausal women 65 to 79 years of age, there was an increased risk of developing probable dementia in the estrogen plus progestin ancillary study when compared to placebo. (See CLINICAL STUDIES and WARNINGS, Probable dementia.)

ADVERSE REACTIONS

See BOXED WARNING, WARNINGS and PRECAUTIONS.

Because clinical trials are conducted under widely varying conditions, adverse reaction rates observed in the clinical trials of a drug cannot be directly compared to rates in the clinical trials of another drug and may not reflect the rates observed in practice.

In a multicenter, randomized, double-blind, placebo-controlled clinical trial, the effects of Progesterone, USP Capsules on the endometrium was studied in a total of 875 postmenopausal women. Table 6 lists adverse reactions greater than or equal to 2 percent of women who received cyclic Progesterone, USP Capsules 200 mg daily (12 days per calendar month cycle) with 0.625 mg conjugated estrogens or placebo.

TABLE 6. Adverse Reactions (≥ 2%) Reported in an 875 Patient Placebo-Controlled Trial in Postmenopausal Women Over a 3-Year Period [Percentage (%) of Patients Reporting]
 | Progesterone, USP Capsules 200 mg with Conjugated Estrogens 0.625 mg | Placebo
 | (n=178) | (n=174)
Headache | 31 | 27
Breast Tenderness | 27 | 6
Joint Pain | 20 | 29
Depression | 19 | 12
Dizziness | 15 | 9
Abdominal Bloating | 12 | 5
Hot Flashes | 11 | 35
Urinary Problems | 11 | 9
Abdominal Pain | 10 | 10
Vaginal Discharge | 10 | 3
Nausea / Vomiting | 8 | 7
Worry | 8 | 4
Chest Pain | 7 | 5
Diarrhea | 7 | 4
Night Sweats | 7 | 17
Breast Pain | 6 | 2
Swelling of Hands and Feet | 6 | 9
Vaginal Dryness | 6 | 10
Constipation | 3 | 2
Breast Carcinoma | 2 | <1
Breast Excisional Biopsy | 2 | <1
Cholecystectomy | 2 | <1

Effects on Secondary Amenorrhea

In a multicenter, randomized, double-blind, placebo-controlled clinical trial, the effects of Progesterone, USP Capsules on secondary amenorrhea was studied in 49 estrogen-primed postmenopausal women. Table 7 lists adverse reactions greater than or equal to 5 percent of women who received Progesterone, USP Capsules or placebo.

TABLE 7. Adverse Reactions (≥ 5%) Reported in Patients Using 400 mg/day in a Placebo-Controlled Trial in Estrogen- Primed Postmenopausal Women
Adverse Experience | Progesterone, USP Capsules 400 mg | Placebo
 | n=25 | n=24
 | Percentage (%) of Patients
Fatigue | 8 | 4
Headache | 16 | 8
Dizziness | 24 | 4
Abdominal Distention (Bloating) | 8 | 8
Abdominal Pain (Cramping) | 20 | 13
Diarrhea | 8 | 4
Nausea | 8 | 0
Back Pain | 8 | 8
Musculoskeletal Pain | 12 | 4
Irritability | 8 | 4
Breast Pain | 16 | 8
Infection Viral | 12 | 0
Coughing | 8 | 0

In a multicenter, parallel-group, open label postmarketing dosing study consisting of three consecutive 28-day treatment cycles, 220 premenopausal women with secondary amenorrhea were randomized to receive daily conjugated estrogens therapy (0.625 mg conjugated estrogens) and Progesterone, USP Capsules, 300 mg per day (n=113) or Progesterone, USP Capsules, 400 mg per /day (n=107) for 10 days of each treatment cycle. Overall, the most frequently reported treatment-emergent adverse reactions, reported in greater than or equal to 5 percent of subjects, were nausea, fatigue, vaginal mycosis, nasopharyngitis, upper respiratory tract infection, headache, dizziness, breast tenderness, abdominal distension, acne, dysmenorrhea, mood swing, and urinary tract infection.

Postmarketing Experience:

The following additional adverse reactions have been reported with Progesterone, USP Capsules. Because these reactions are reported voluntarily from a population of uncertain size, it is not always possible to reliably estimate the frequency or establish a causal relationship to drug exposure.

Genitourinary System: endometrial carcinoma, hypospadia, intra-uterine death, menorrhagia, menstrual disorder, metrorrhagia, ovarian cyst, spontaneous abortion.

Cardiovascular: circulatory collapse, congenital heart disease (including ventricular septal defect and patent ductus arteriosus), hypertension, hypotension, tachycardia.

Gastrointestinal: acute pancreatitis, cholestasis, cholestatic hepatitis, dysphagia, hepatic failure, hepatic necrosis, hepatitis, increased liver function tests (including alanine aminotransferase increased, aspartate aminotransferase increased, gamma-glutamyl transferase increased), jaundice, swollen tongue.

Skin: alopecia, pruritus, urticaria.

Eyes: blurred vision, diplopia, visual disturbance.

Central Nervous System: aggression, convulsion, depersonalization, depressed consciousness, disorientation, dysarthria, loss of consciousness, paresthesia, sedation, stupor, syncope (with and without hypotension), transient ischemic attack, suicidal ideation.

During initial therapy, a few women have experienced a constellation of many or all of the following symptoms: extreme dizziness and/or drowsiness, blurred vision, slurred speech, difficulty walking, loss of consciousness, vertigo, confusion, disorientation, feeling drunk, and shortness of breath.

Miscellaneous: abnormal gait, anaphylactic reaction, arthralgia, blood glucose increased, choking, cleft lip, cleft palate, difficulty walking, dyspnea, face edema, feeling abnormal, feeling drunk, hypersensitivity, asthma, muscle cramp, throat tightness, tinnitus, vertigo, weight decreased, weight increased.

OVERDOSAGE

No studies on overdosage have been conducted in humans. In the case of overdosage, Progesterone, USP Capsules should be discontinued and the patient should be treated symptomatically.

DOSAGE AND ADMINISTRATION

Prevention of Endometrial Hyperplasia

Progesterone, USP Capsules should be given as a single daily dose at bedtime, 200 mg orally for 12 days sequentially per 28-day cycle, to a postmenopausal woman with a uterus who is receiving daily conjugated estrogens tablets.

Treatment of Secondary Amenorrhea

Progesterone, USP Capsules may be given as a single daily dose of 400 mg at bedtime for 10 days.

Some women may experience difficulty swallowing Progesterone, USP Capsules. For these women, Progesterone, USP Capsules should be taken with a glass of water while in the standing position.

HOW SUPPLIED

Product: 50090-3240

NDC: 50090-3240-0 10 CAPSULE in a BOTTLE

NDC: 50090-3240-1 90 CAPSULE in a BOTTLE

Distributed by:
Virtus Pharmaceuticals, LLC
Langhorne, PA 19047
1-888-848-3593

9923 Rev. 04/2020

PATIENT INFORMATION

Progesterone, USP
Capsules 100 mg
Capsules 200 mg
Rx only

Read this PATIENT INFORMATION before you start taking Progesterone, USP Capsules and read what you get each time you refill your Progesterone, USP Capsules prescription. There may be new information. This information does not take the place of talking to your healthcare provider about your medical condition or your treatment.

WHAT IS THE MOST IMPORTANT INFORMATION I SHOULD KNOW ABOUT Progesterone, USP CAPSULES (A Progesterone Hormone)?

- Progestins with estrogens should not be used to prevent heart disease, heart attacks, strokes, or dementia.
- Using progestins with estrogens may increase your chance of getting heart attacks, strokes, breast cancer, and blood clots.
- Using progestins with estrogens may increase your chance of getting dementia, based on a study of women age 65 and older.
- You and your healthcare provider should talk regularly about whether you still need treatment with Progesterone, USP Capsules.

THIS PRODUCT CONTAINS PEANUT OIL AND SHOULD NOT BE USED IF YOU ARE ALLERGIC TO PEANUTS.

What is Progesterone, USP Capsules?
Progesterone, USP Capsules contain the female hormone called progesterone.

What is Progesterone, USP Capsules used for?
Treatment of Menstrual Irregularities
Progesterone, USP Capsules are used for the treatment of secondary amenorrhea (absence of menstrual periods in women who have previously had a menstrual period) due to a decrease in progesterone. When you do not produce enough progesterone, menstrual irregularities can occur. If your healthcare provider has determined your body does not produce enough progesterone on its own, Progesterone, USP Capsules may be prescribed to provide the progesterone you need.

Protection of the Endometrium (Lining of the Uterus)
Progesterone, USP Capsules are used in combination with estrogen-containing medications in a postmenopausal woman with a uterus (womb). Taking estrogen-alone increases the chance of developing a condition called endometrial hyperplasia that may lead to cancer of the lining of the uterus (womb). The addition of a progestin is generally recommended for a woman with a uterus to reduce the chance of getting cancer of the uterus (womb).

Who should not take Progesterone, USP Capsules?
Do not start taking Progesterone, USP Capsules if you:

- Are allergic to peanuts
- Have unusual vaginal bleeding
- Currently have or have had certain cancers
  Estrogen plus progestin treatment may increase the chance of getting certain types of cancers, including cancer of the breast or uterus. If you have or have had cancer, talk with your healthcare provider about whether you should take Progesterone, USP Capsules.
- Had a stroke or heart attack
- Currently have or have had blood clots
- Currently have or have had liver problems
- Are allergic to Progesterone, USP Capsules or any of its ingredients
  See the list of ingredients in Progesterone, USP Capsules at the end of this leaflet.
- Think you may be pregnant

Tell your healthcare provider:

- If you are breastfeeding. The hormone in Progesterone, USP Capsules can pass into your breast milk.
- About all of your medical problems. Your healthcare provider may need to check you more carefully if you have certain conditions, such as asthma (wheezing), epilepsy (seizures), diabetes, migraine, endometriosis, lupus, problems with your heart, liver, thyroid, or kidneys, or have high calcium levels in your blood.
- About all the medicines you take. This includes prescription and nonprescription medicines, vitamins, and herbal supplements. Some medicines may affect how Progesterone, USP Capsules work. Progesterone, USP Capsules may also affect how your other medicines work.

How should I take Progesterone, USP Capsules?

1. Prevention of Endometrial Hyperplasia: A post-menopausal woman with a uterus who is taking estrogens should take a single daily dose of 200 mg Progesterone, USP Capsules at bedtime for 12 continuous days per 28-day cycle.
2. Secondary Amenorrhea: Progesterone, USP Capsules may be given as a single daily dose of 400 mg at bedtime for 10 days.
3. Progesterone, USP Capsules are to be taken at bedtime as some women become very drowsy and/or dizzy after taking Progesterone, USP Capsules. In a few cases, symptoms may include blurred vision, difficulty speaking, difficulty with walking, and feeling abnormal. If you experience these symptoms, discuss them with your healthcare provider right away.
4. If you experience difficulty in swallowing Progesterone, USP Capsules, it is recommended that you take your daily dose at bedtime with a glass of water while in the standing position.

What are the possible side effects of Progesterone, USP Capsules?
Side effects are grouped by how serious they are and how often they happen when you are treated:

Serious, but less common side effects include:

- Risk to the Fetus: Cases of cleft palate, cleft lip, hypospadias, ventricular septal defect, patent ductus arteriosus, and other congenital heart defects.
- Abnormal Blood Clotting: Stroke, heart attack, pulmonary embolus, visual loss or blindness.

Some of the warning signs of serious side effects include:

- Changes in vision or speech
- Sudden new severe headaches
- Severe pains in your chest or legs with or without shortness of breath, weakness and fatigue
- Dizziness and faintness
- Vomiting

Call your healthcare provider right away if you get any of these warning signs, or any other unusual symptoms that concern you.

Less serious, but common side effects include:

- Headaches
- Breast pain
- Irregular vaginal bleeding or spotting
- Stomach or abdominal cramps, bloating
- Nausea and vomiting
- Hair loss
- Fluid retention
- Vaginal yeast infection

These are not all the possible side effects of Progesterone, USP Capsules. For more information, ask your healthcare provider or pharmacist for advice about side effects. You may report side effects to Virtus Pharmaceuticals, LLC. at 1-888-848-3593 or to FDA at 1-800-FDA-1088.

What can I do to lower my chances of getting a serious side effect with Progesterone, USP Capsules?

- Talk with your healthcare provider regularly about whether you should continue taking Progesterone, USP Capsules.
- See your healthcare provider right away if you get unusual vaginal bleeding while taking Progesterone, USP Capsules.
- Have a pelvic exam, breast exam, and mammogram (breast X-ray) every year unless your healthcare provider tells you something else. If members of your family have had breast cancer or if you have ever had breast lumps or an abnormal mammogram, you may need to have breast exams more often.
- If you have high blood pressure, high cholesterol (fat in the blood), diabetes, are overweight, or if you use tobacco, you may have higher chances for getting heart disease. Ask your healthcare provider for ways to lower your chances for getting heart disease.

General information about safe and effective use of Progesterone, USP Capsules

- Medicines are sometimes prescribed for conditions that are not mentioned in patient information leaflets. Do not take Progesterone, USP Capsules for conditions for which it was not prescribed.
- Your healthcare provider has prescribed this drug for you and you alone. Do not give Progesterone, USP Capsules to other people, even if they have the same symptoms you have. It may harm them.
- Progesterone, USP Capsules should be taken as a single daily dose at bedtime. Some women may experience extreme dizziness and/or drowsiness during initial therapy. In a few cases, symptoms may include blurred vision, difficulty speaking, difficulty with walking, and feeling abnormal. If you experience these symptoms, discuss them with your healthcare provider right away.
- Use caution when driving a motor vehicle or operating machinery as dizziness or drowsiness may occur.

Keep Progesterone, USP Capsules out of the reach of children.

This leaflet provides a summary of the most important information about Progesterone, USP Capsules. If you would like more information, talk with your healthcare provider or pharmacist. You can ask for information about Progesterone, USP Capsules that is written for health professionals. You can get more information by calling the toll free number 1-888-848-3593.

What are the ingredients in Progesterone, USP Capsules?
Active ingredient: 100 mg or 200 mg micronized progesterone
The inactive ingredients for Progesterone, USP Capsules 100 mg include: peanut oil NF, gelatin NF, glycerin USP, lecithin NF, titanium dioxide USP, FD&C Red No. 40, and D&C Yellow No. 10.
The inactive ingredients for Progesterone, USP Capsules 200 mg include: peanut oil NF, gelatin NF, glycerin USP, lecithin NF, titanium dioxide USP, D&C Yellow No. 10, and FD&C Yellow No. 6.

HOW SUPPLIED

Progesterone, USP Capsules 100 mg are round, peach-colored capsules branded with black imprint "SV."

Progesterone, USP Capsules 200 mg are oval, pale yellow-colored capsules branded with black imprint "SV2."

Store at 25°C (77°F); excursions permitted to 15° to 30°C (59° to 86°F) [See USP Controlled Room Temperature].

Protect from excessive moisture.

Distributed by:
Virtus Pharmaceuticals, LLC.
Langhorne, PA 19047
1-888-848-3593
9924 Rev. 04/2020.1